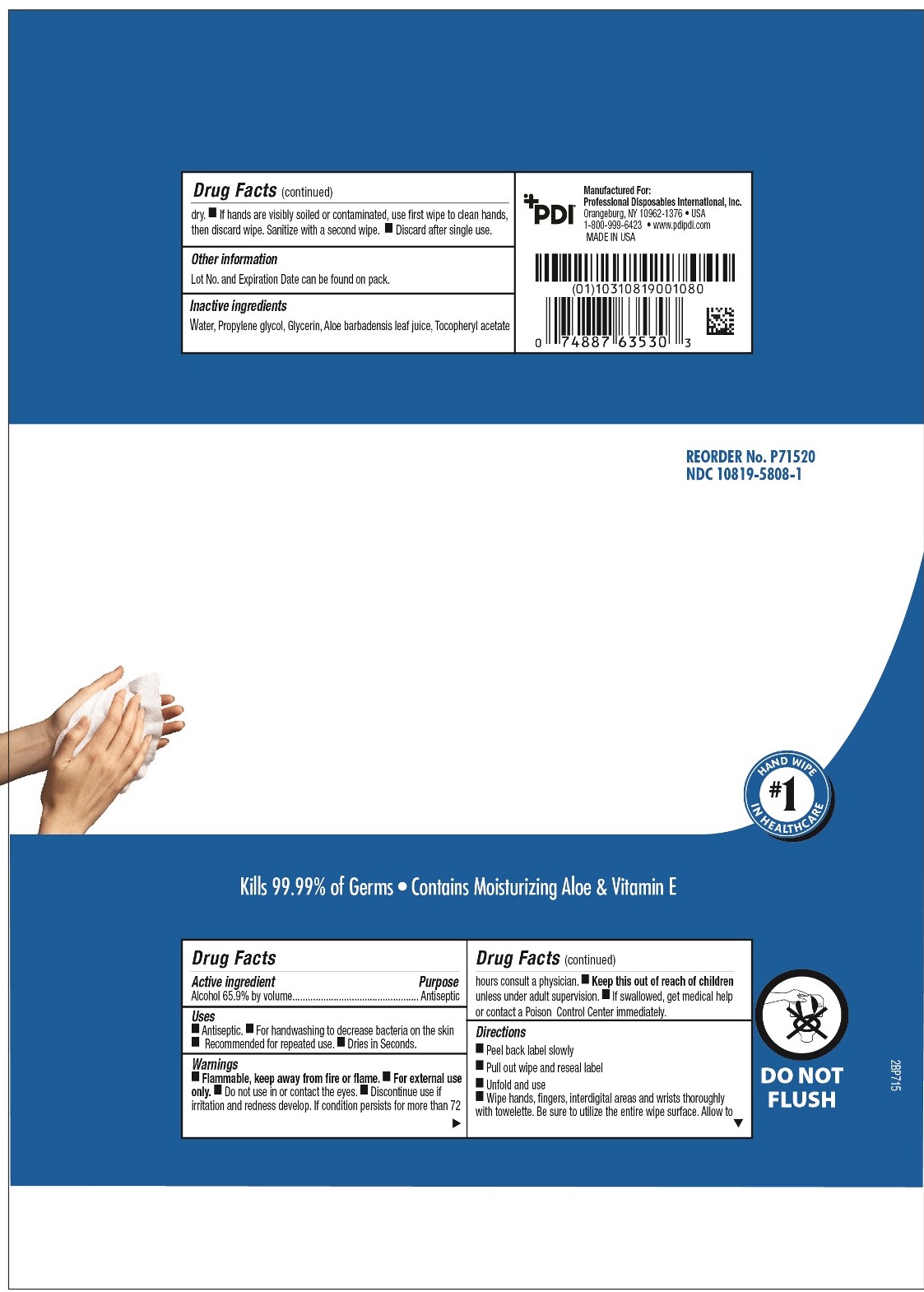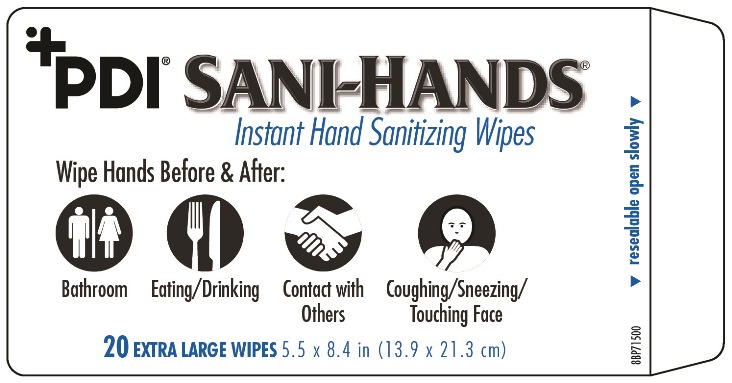 DRUG LABEL: PDI Sani-Hands Instant Hand Sanitizing Wipes
NDC: 10819-5808 | Form: CLOTH
Manufacturer: Professional Disposables International, Inc.
Category: otc | Type: HUMAN OTC DRUG LABEL
Date: 20151223

ACTIVE INGREDIENTS: ALCOHOL 0.659 mL/1 mL
INACTIVE INGREDIENTS: WATER; PROPYLENE GLYCOL; GLYCERIN; ALOE VERA LEAF; ALPHA-TOCOPHEROL ACETATE

bedside pack 65.9% NDC 10819-5808-1

Uses

- Antiseptic
- For hand washing to decrease bacteria on the skin.
- Recommended for repeated use.
- Dries in seconds.

Warnings

- Flammable, keep away from fire or flame.
- For external use only.
- Do not use in or contact the eyes.
- Discontinue use if irritation and redness develop. If condition persist for more than 72 hours consult a physician.
- If swallowed, get medical help or contact a Poison Control Center immediately.

Keep out of reach of children

unless under adult supervision.

Directions

- Peel back label slowly
- Pull out wipe and reseal label
- Unfold and use
- Wipe hands, fingers, interdigital areas and wrists thoroughly with towelettes. Be sure to utilize the entire wipe surface. Allow to dry.
- If hands are visibly soiled or contaminated, use first wipe to clean hands, then discard wipe. Sanitize with a second wipe.
- Discard after single use.

Other information

Lot No. and Expiration Date can be found on pack.

Dosage

Use first wipe to clean hands, then discard wipe. Sanitize with a second wipe.

Inactive ingredients

Water, Propylene Glycol, Glycerin, Aloe Barbadensis Leaf Juice, Tocopheryl Acetate

Manufactured for:

Professional Disposables International, Inc.
Orangeburg, NY 10962-1376 - USA - 1-800-999-6423
Made in USA

www.pdipdi.com

Active ingredient

Alcohol 65.9% by volume

Purpose

Antiseptic

Principal Display Panel - 20 Count

lid:

flowrap: